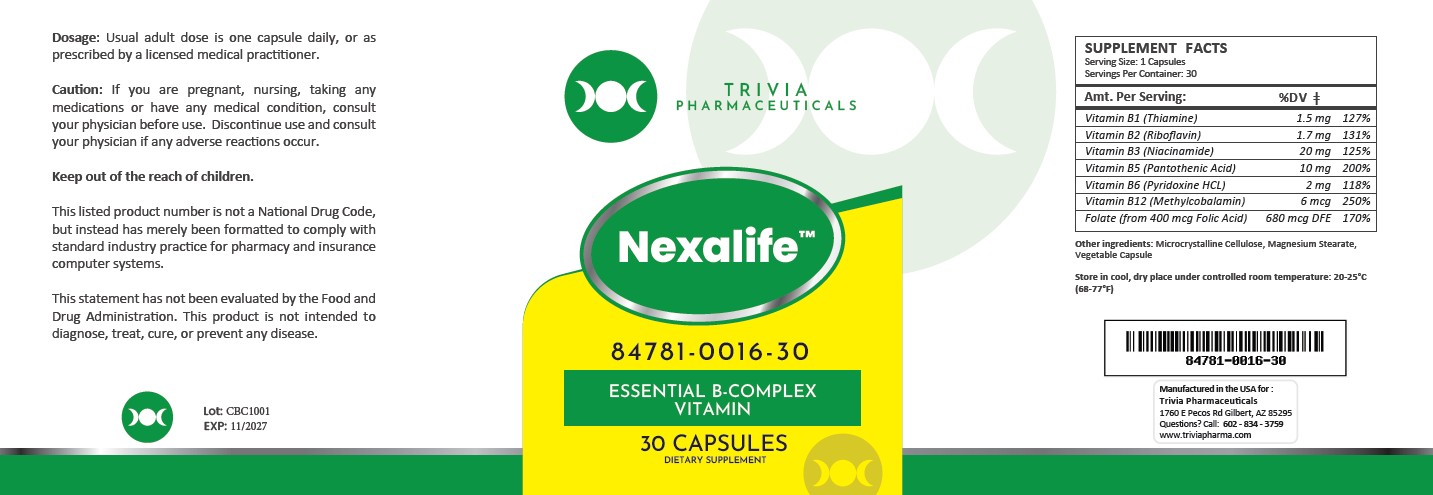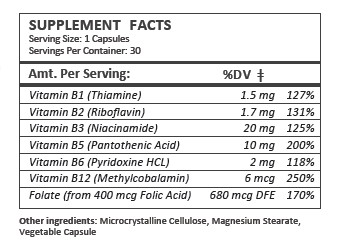 DRUG LABEL: Nexalife
NDC: 84781-016 | Form: CAPSULE
Manufacturer: Trivia Pharmaceuticals, LLC
Category: other | Type: Dietary Supplement
Date: 20250813

ACTIVE INGREDIENTS: THIAMINE HCL 1.5 mg/1 1; RIBOFLAVIN 1.7 mg/1 1; NIACINAMIDE 20 mg/1 1; PANTOTHENIC ACID 10 mg/1 1; PYRIDOXINE HYDROCHLORIDE 2 mg/1 1; METHYLCOBALAMIN 6 ug/1 1; FOLIC ACID 680 ug/1 1
INACTIVE INGREDIENTS: MICROCRYSTALLINE CELLULOSE; MAGNESIUM STEARATE

Nexalife

Health Claim Section:

Nexalife B-Complex Vitamin Capsules

Description:

Nexalife B-Complex Capsules are supplied as clear capsules dispensed in plastic bottles of 30 ct.

84781-0016-30

Reserved for Professional Recommendation

This listed product is not a National Drug Code, but instead has merely been formatted to comply with standard industry practice for pharmacy and insurance computer systems.

All prescriptions using this product shall be pursuant to state statutes as applicable. This is not an Orange Book product. This product may be administered only under a physician’s supervision. There are no implied or explicit claims on therapeutic equivalence.

Manufactured for:
Trivia Pharmaceuticals

Gilbert, AZ

Warnings and Precautions:

This product is contraindicated in patients with a known hypersensitivity to any of the ingredients.

As with any supplement, if you are pregnant, nursing, taking medication, or have a medical condition, ask a health professional before taking this product.

These statements have not been evaluated by the Food and Drug Administration. This product is not intended to diagnose, treat, cure, or prevent any disease.

Dosage and Administration:

Usual adult dose is 1 capsule by mouth daily once daily, or as prescribed by a licensed medical practitioner.

Nexalife capsules is an orally administered prescription vitamin to provide significant amounts of B Vitamins and folate to supplement the diet, and to help assure that nutritional deficiencies of these vitamines will not develop.

How Supplied:

CONTRAINDICATIONS
This product is contraindicated in patients with known hypersensitivity to any of the ingredients.

PRECAUTIONS
This product is contraindicated in patients with a known hypersensitivity to any of the ingredients.

ADVERSE REACTIONS
Allergic sensitizations have been reported following oral administration of folic acid. Consult your physician immediately if adverse side effects occur.

KEEP OUT OF THE REACH OF CHILDREN.

Storage:

Store at 20° to 25°C (68° to 77°F); excursions permitted to 15° to 30°C (59° to 86°F). [See USP Controlled Room Temperature.] Protect from light and moisture.